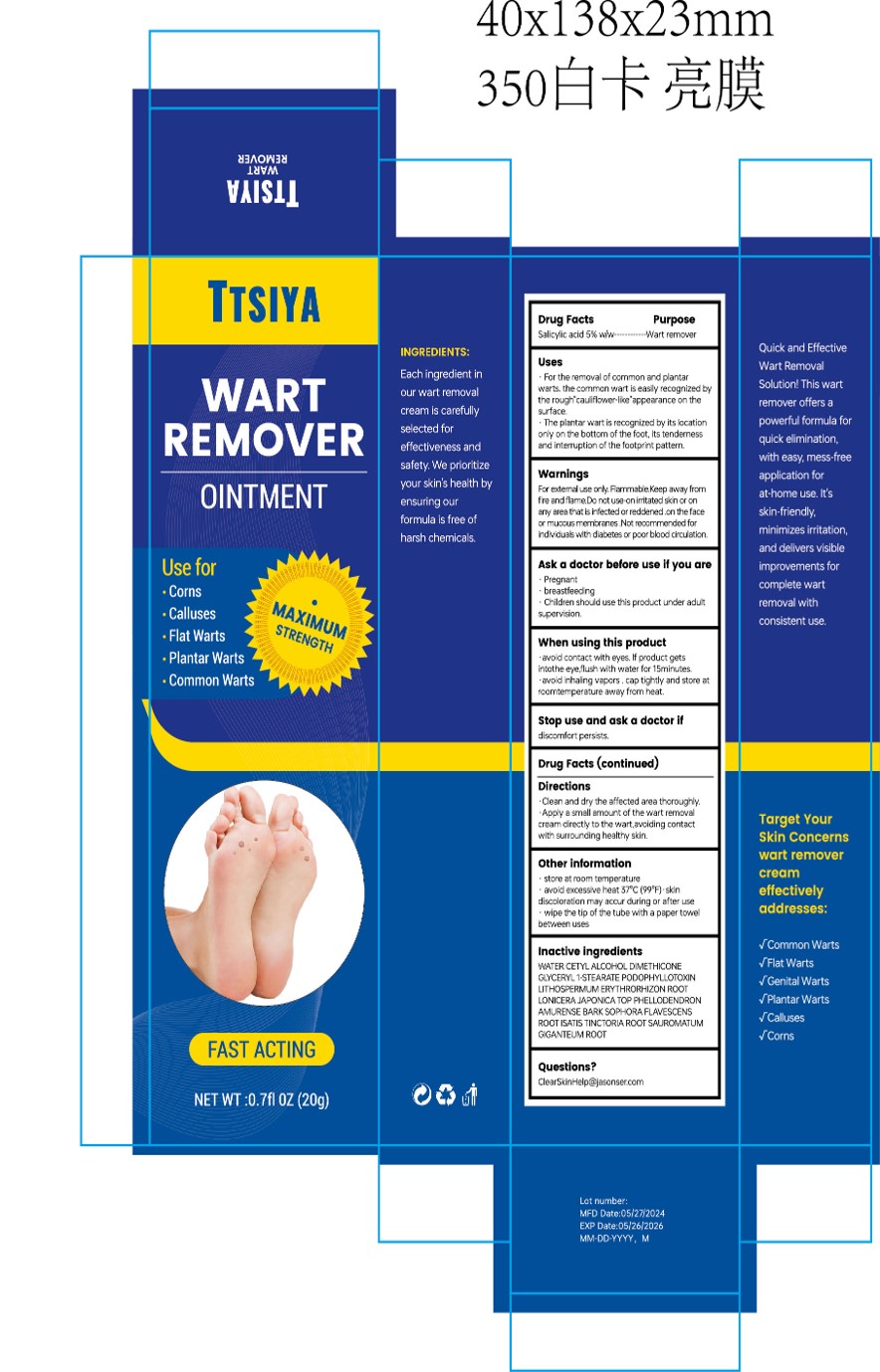 DRUG LABEL: TTSIYA WART REMOVER
NDC: 84867-007 | Form: CREAM
Manufacturer: Jiashen International Trading Co., Ltd.
Category: otc | Type: HUMAN OTC DRUG LABEL
Date: 20251109

ACTIVE INGREDIENTS: SALICYLIC ACID 100 mg/20 g
INACTIVE INGREDIENTS: DIMETHICONE; GLYCERYL 1-STEARATE; SOPHORA FLAVESCENS ROOT; SAUROMATUM GIGANTEUM ROOT; WATER; LONICERA JAPONICA TOP; PODOFILOX; CETYL ALCOHOL; PHELLODENDRON AMURENSE BARK; LITHOSPERMUM ERYTHRORHIZON ROOT; ISATIS TINCTORIA ROOT

ACTIVE INGREDIENT

Salicylic acid 5% w/w

INACTIVE INGREDIENT

Water
Cetyl Alcohol
Dimethicone
Glyceryl 1-stearate
Podophyllotoxin
LITHOSPERMUM ERYTHRORHIZON ROOT
LONICERA JAPONICA TOP
PHELLODENDRON AMURENSE BARK
SOPHORA FLAVESCENS ROOT
ISATIS TINCTORIA ROOT
SAUROMATUM GIGANTEUM ROOT

PURPOSE

Quick and EffectiveWart RemovalSolution this is wartremover offers a
powerful formula forquick elimination,with easy, mess-freeapplication forat-home use. lt'sskin-friendly,minimizes irritation,and delivers visibleimprovements forcomplete wartremoval withconsistent use.

Warnings
For exteral use only. Flammable.Keep away fromfire and flame.Do not use on irritated skin or onany area that is infected or reddened .on the faceor mucous membranes .Not recommended forindividuals with diabetes or poor blood circulation.

Ask a doctor before use if you are
Pregnant
breastfeeding
Children should use this product under adult
supervision.

Stop use and ask a doctor if discomfort persists.

Keep out of reach of children.Children should use this product under adultsupervision.

WHEN USING

When using this productavoid contact with eyes. lf product getsintothe eye,flush with water for 15minutes,·avoid inhaling vapors . cap tightly and store atroomtemperature away from heat.

Directions
.Clean and dry the affected area thoroughly.Apply a small amount of the wart removalcream directly to the wart,avoiding contactwith surrounding healthy skin.

Uses

Take an appropriate amount.
. For the removal of common and plantarwarts. the common wart is easily recognized bythe rough"cauliflower-like"appearance on thesurface.
The plantar wart is recognized by its locationonly on the bottom of the foot, its tendernessand interruption of the footprint pattern.